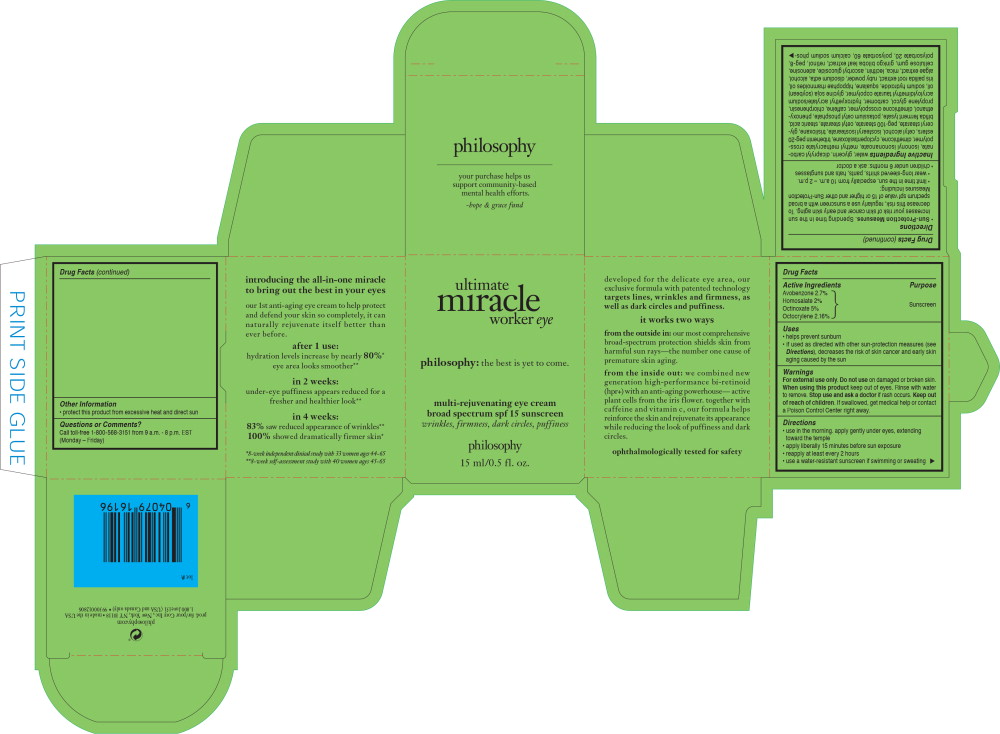 DRUG LABEL: ultimate miracle worker eye spf 15
NDC: 50184-1012 | Form: CREAM
Manufacturer: Philosophy, Inc.
Category: otc | Type: HUMAN OTC DRUG LABEL
Date: 20230128

ACTIVE INGREDIENTS: AVOBENZONE 2.7 g/100 mL; HOMOSALATE 2 g/100 mL; OCTINOXATE 5 g/100 mL; OCTOCRYLENE 2.16 g/100 mL
INACTIVE INGREDIENTS: CAPRYLYL GLYCOL; BETASIZOFIRAN; BUTYLATED HYDROXYANISOLE; SORBIC ACID; TITANIUM DIOXIDE; WATER; GLYCERIN; DICAPRYLYL CARBONATE; ISONONYL ISONONANOATE; DIMETHICONE; CYCLOMETHICONE 5; TRIBEHENIN PEG-20 ESTERS; CETYL ALCOHOL; ISOSTEARYL ISOSTEARATE; TRISILOXANE; GLYCERYL MONOSTEARATE; PEG-100 STEARATE; CETYL STEARATE; STEARIC ACID; POTASSIUM CETYL PHOSPHATE; PHENOXYETHANOL; DIMETHICONE CROSSPOLYMER (450000 MPA.S AT 12% IN CYCLOPENTASILOXANE); CAFFEINE; CHLORPHENESIN; PROPYLENE GLYCOL; CARBOXYPOLYMETHYLENE; HYDROXYETHYL ACRYLATE/SODIUM ACRYLOYLDIMETHYL TAURATE COPOLYMER (100000 MPA.S AT 1.5%); SOYBEAN OIL; SODIUM HYDROXIDE; SQUALANE; EDETATE DISODIUM ANHYDROUS; ALCOHOL; MICA; LECITHIN, SOYBEAN; ASCORBYL GLUCOSIDE; ADENOSINE; CARBOXYMETHYLCELLULOSE SODIUM, UNSPECIFIED FORM; GINKGO; RETINOL; POLYETHYLENE GLYCOL 400; POLYSORBATE 20; POLYSORBATE 60; BUTYLATED HYDROXYTOLUENE; CARBOMER COPOLYMER TYPE A (ALLYL PENTAERYTHRITOL CROSSLINKED); POLIGLUSAM; ETHYLHEXYLGLYCERIN; GLYCOLIC ACID; SORBITAN MONOOLEATE; TOCOPHEROL; HORSE CHESTNUT; DEXTROSE, UNSPECIFIED FORM; LACTIC ACID, UNSPECIFIED FORM; BEHENTRIMONIUM CHLORIDE; GLYCYRRHIZA URALENSIS; SODIUM BENZOATE; ASCORBYL PALMITATE; POTASSIUM PHOSPHATE, UNSPECIFIED FORM; POTASSIUM SORBATE; GREEN TEA LEAF; ARABICA COFFEE BEAN; MILLETTIA PINNATA SEED; ISOPROPYL ALCOHOL; ACETIC ACID; CITRUS AURANTIUM FRUIT RIND; MALTODEXTRIN; CITRIC ACID MONOHYDRATE; MAGNESIUM ALUMINUM SILICATE; XANTHAN GUM; ASCORBIC ACID

Ultimate Miracle Worker Eye

Drug Facts

Active Ingredients

Avobenzone 2.7%

Homosalate 2%

Octinoxate 5%

Octocrylene 2.16%

Purpose

Sunscreen

Uses

- helps prevent sunburn
- if used as directed with other sun-protection measures (see Directions), decreases the risk of skin cancer and early skin aging caused by the sun

Warnings

For external use only.

Do not use on damaged or broken skin.

When using this product keep out of eyes. Rinse with water to remove.

Stop use and ask a doctor if rash occurs.

Keep out of reach of children. If swallowed, get medical help or contact a Poison Control Center right away.

Directions

- use in the morning. apply gently under eyes, extending toward the temple
- apply liberally 15 minutes before sun exposure
- reapply at least every 2 hours
- use a water-resistant sunscreen if swimming or sweating
- Directions
- Sun-Protection Measures. Spending time in the sun increases your risk of skin cancer and early skin aging. To decrease this risk, regularly use a sunscreen with a broad spectrum spf value of 15 or higher and other Sun-Protection Measures including:
  - limit time in the sun, especially from 10 a.m. – 2 p.m.
  - wear long-sleeved shirts, pants, hats and sunglasses
- children under 6 months: ask a doctor

Inactive Ingredients

water, glycerin, dicaprylyl carbonate, isononyl isononanoate, methyl methacrylate crosspolymer, dimethicone, cyclopentasiloxane, tribehenin peg-20 esters, cetyl alcohol, isostearyl isostearate, trisiloxane, glyceryl stearate, peg-100 stearate, cetyl stearate, stearic acid, bifida ferment lysate, potassium cetyl phosphate, phenoxyethanol, dimethicone crosspolymer, caffeine, chlorphenesin, propylene glycol, carbomer, hydroxyethyl acrylate/sodium acryloyldimethyl taurate copolymer, glycine soja (soybean) oil, sodium hydroxide, squalane, hippophae rhamnoides oil, iris pallida root extract, ruby powder, disodium edta, alcohol, algae extract, mica, lecithin, ascorbyl glucoside, adenosine, cellulose gum, ginkgo biloba leaf extract, retinol, peg-8, polysorbate 20, polysorbate 60, calcium sodium phos-phosilicate, bht, acrylates/c10-30 alkyl acrylate crosspolymer, chitosan, ethylhexylglycerin, glycolic acid, sorbitan oleate, tocopherol, aesculus hippocastanum (horse chestnut) seed extract, glucose, lactic acid, behentrimonium chloride, glycyrrhiza uralensis (licorice) root extract, sodium benzoate, ascorbyl palmitate, potassium phosphate, potassium sorbate, camellia sinensis leaf extract, coffea arabica (coffee) seed extract, pongamia pinnata seed extract, isopropyl alcohol, acetic acid, angelica archangelica root extract, citrus aurantium amara (bitter orange) peel extract, maltodextrin, citric acid, magnesium aluminum silicate, xanthan gum, ascorbic acid, glycyrrhiza glabra (licorice) rhizome/root extract, glycyrrhiza glabra (licorice) root extract, caprylyl glycol, sclerotium gum, bha, sorbic acid, titanium dioxide (ci 77891).

Other Information

- protect this product from excessive heat and direct sun

Questions or Comments?

Call toll-free 1-800-568-3151 from 9 a.m. - 8 p.m. EST (Monday – Friday)

Principal Display Panel - Ultimate Miracle Worker Eye Carton Label

ultimate
miracle
worker eye

philosophy: the best is yet to come.

multi-rejuvenating eye cream
broad spectrum spf 15 sunscreen

wrinkles, firmness, dark circles, puffiness

philosophy

15 ml/0.5 fl. oz.